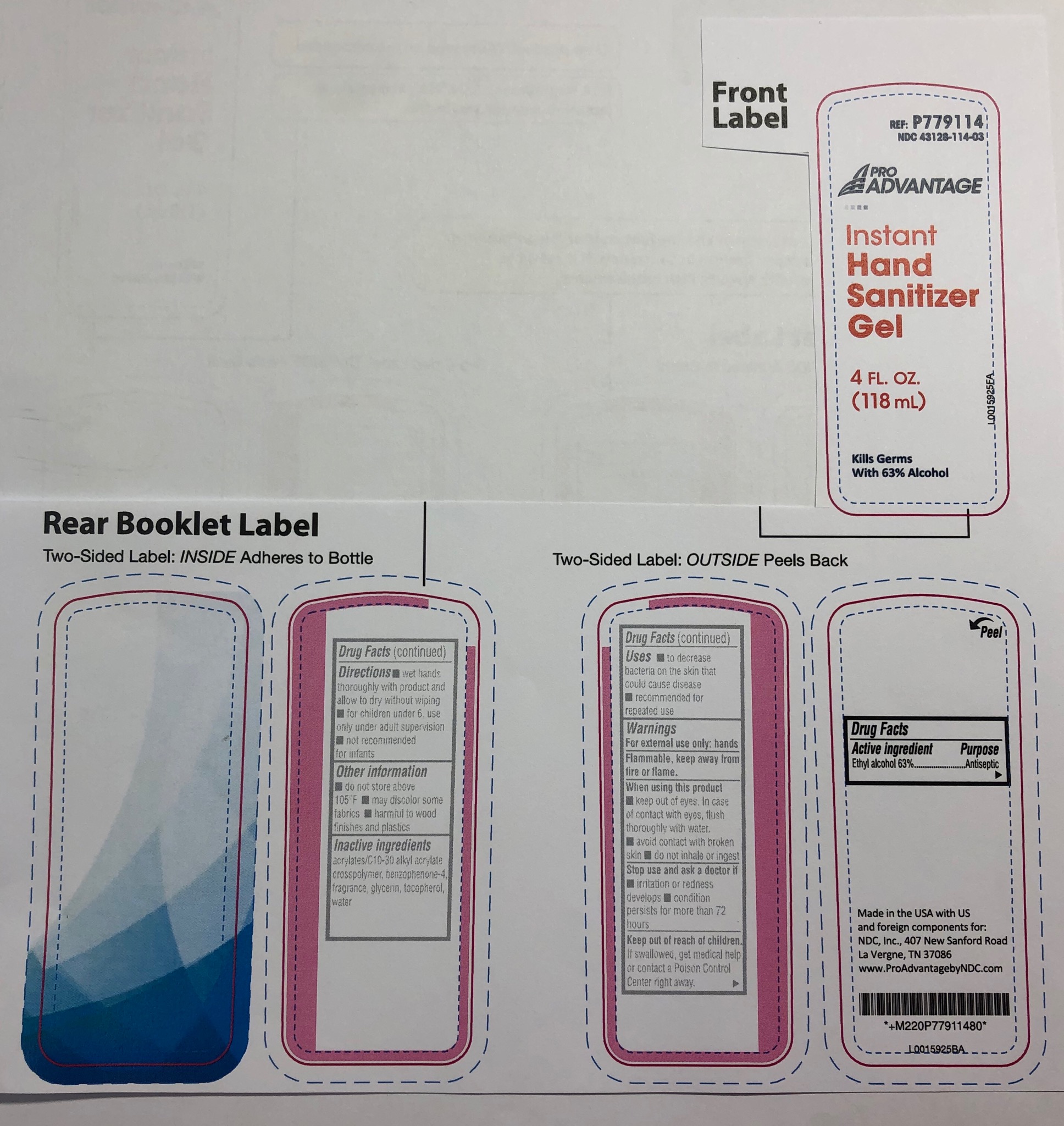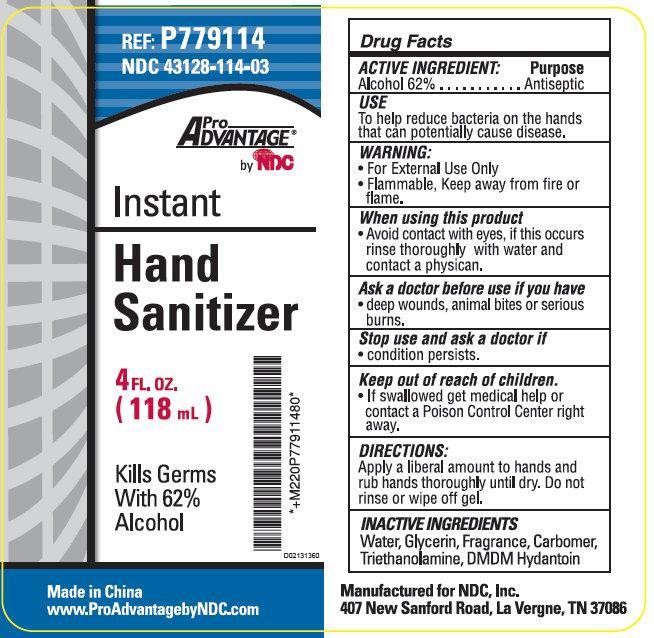 DRUG LABEL: Pro Advantage Instant Hand Sanitizer
NDC: 43128-114 | Form: LIQUID
Manufacturer: NDC National Distribution & Contracting, Inc.
Category: otc | Type: HUMAN OTC DRUG LABEL
Date: 20230315

ACTIVE INGREDIENTS: ALCOHOL 620 mg/1 mL
INACTIVE INGREDIENTS: WATER; GLYCERIN; TROLAMINE; DMDM HYDANTOIN

Pro Advantage Instant Hand Sanitizer

ACTIVE INGREDIENT:

Alcohol, 62%

Purpose

Antiseptic

USE

To help reduce bacteria on the hands that can potentially cause disease.

WARNING:

• For External Use Only
• Flammable, Keep away from fire or flame.

When using this product

• Avoid contact with eyes, if this occurs rinse thoroughly with water and contact a physician.

Ask a doctor before use if you have

• deep wounds, animals bites or serious burns.

Stop use and ask a doctor if

• condition persists.

Keep out of reach of children.

• If swallowed get medical help or contact a Poison Control Center right away.

DIRECTIONS:

Apply a liberal amount to hands and rub hands thoroughly until dry. Do not rinse or wipe off gel.

INACTIVE INGREDIENTS

Water, Glycerin, Fragrance, Carbomer, Triethanolamine, DMDM Hydantoin

REF: P779114 NDC 43128-114-03

Made in China
www.ProAdvantagebyNDC.com
Manufactured for NDC, Inc.
407 New Sanford Road, La Vergne, TN 37086

PACKAGE LABEL

Pro Advantage by NDC Instant
Hand Sanitizer
4 FL. OZ.
(118 mL)
Kills Germs With 62% Alcohol
*+M220P77911480*